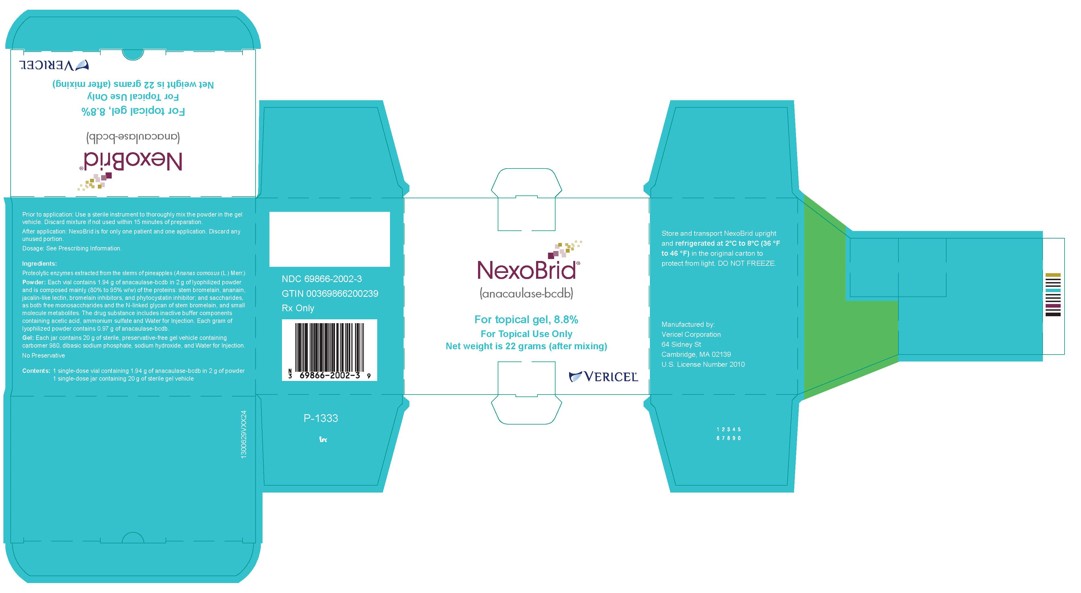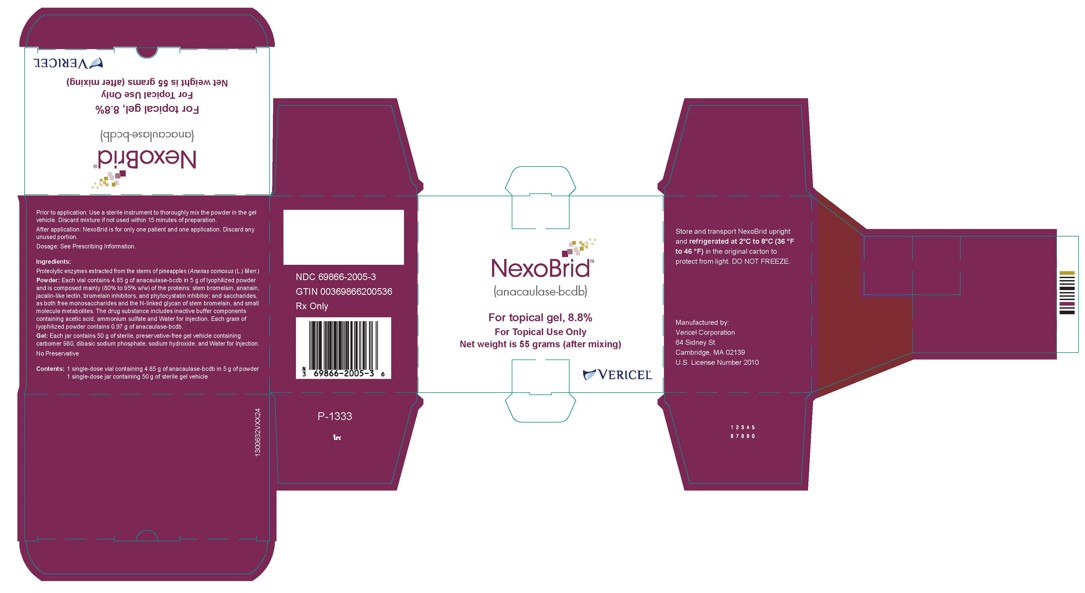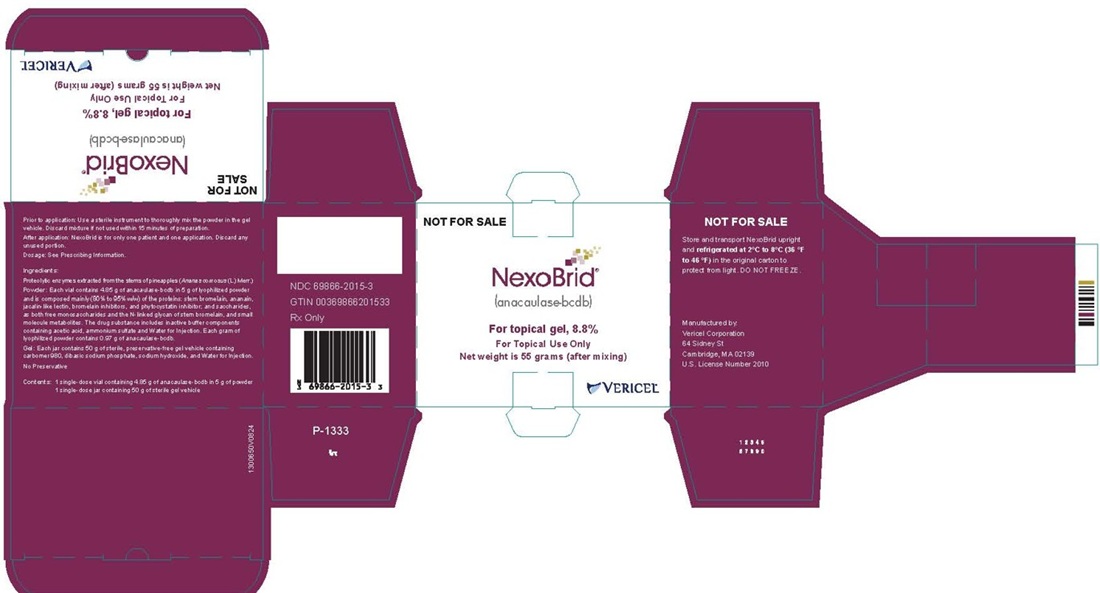 DRUG LABEL: NEXOBRID
NDC: 69866-2002 | Form: KIT | Route: TOPICAL
Manufacturer: Vericel Corporation
Category: prescription | Type: HUMAN PRESCRIPTION DRUG LABEL
Date: 20250911

ACTIVE INGREDIENTS: ANACAULASE-BCDB 158 mg/1 g
INACTIVE INGREDIENTS: ACETIC ACID; AMMONIUM SULFATE; WATER; WATER; CARBOMER HOMOPOLYMER TYPE C (ALLYL PENTAERYTHRITOL CROSSLINKED); SODIUM PHOSPHATE, DIBASIC, ANHYDROUS; SODIUM HYDROXIDE

HIGHLIGHTS OF PRESCRIBING INFORMATION

These highlights do not include all the information needed to use NEXOBRID safely and effectively. See full prescribing information for NEXOBRID.
NEXOBRID® (anacaulase-bcdb), for topical gel
Initial U.S. Approval: 2022

1 INDICATIONS AND USAGE

NEXOBRID contains proteolytic enzymes and is indicated for eschar removal in adults and pediatric patients with deep partial thickness and/or full thickness thermal burns (1).

Limitations of Use

The safety and effectiveness of NEXOBRID have not been established for treatment of:

- Chemical or electrical burns (1).
- Burns on the face, perineum, or genitalia (1).
- Burns on the feet of patients with diabetes mellitus or on the feet of patients with occlusive vascular disease (1).
- Circumferential burns (1).
- Burns in patients with significant cardiopulmonary disease, including inhalation injury (1).

NEXOBRID is not recommended for:

- Wounds contaminated with radioactive and other hazardous substances to avoid unforeseeable reactions with the product and an increased risk of spreading the noxious substance (1)
- Treatment of burn wounds where medical devices (e.g., implants, pacemakers, shunts) or vital structures (e.g., large vessels) could become exposed during eschar removal (1).

2 DOSAGE AND ADMINISTRATION

- NEXOBRID lyophilized powder and gel vehicle must be mixed prior to administration (2.1).
- Use 2 g of Nexobrid lyophilized powder mixed with 20 g gel for treatment of up to 180 cm2 of treated burn area; or 5 g of Nexobrid lyophilized powder mixed with 50 g gel for treatment of up to 450 cm2 of treated burn area (2.1).
- For topical use only (2.1).

- Dosage in Adults:

Apply a 3 mm thick layer of NEXOBRID in one application to an area of up to 15% body surface area (BSA) for four hours. A second application may be applied 24 hours later. For both applications, the total treated area must not exceed 20% BSA (2.2).

- Dosage in Pediatric Patients 6 Years of Age and Older:

Apply a 3 mm thick layer of NEXOBRID in one application of 4 hours to an area of up to 15% BSA (2.2).

- Dosage in Pediatric Patients Less Than 6 Years of Age:

Apply a 3 mm thick layer of NEXOBRID in one application of 4 hours to an area of up to 10% BSA (2.2).

- Prepare NEXOBRID at patient’s bedside within 15 minutes of intended application (2.4).
- Apply NEXOBRID to a clean, moist wound bed free of burned epidermis layer and blisters, and cover with an occlusive film dressing (2.3, 2.4).
- See Full Prescribing Information for additional details on preparation, administration, and removal of NEXOBRID (2.5, 2.6).

3 DOSAGE FORMS AND STRENGTHS

- For topical gel: 8.8% (3).

4 CONTRAINDICATIONS

- Known hypersensitivity to anacaulase-bcdb, bromelain, pineapples, or to any of the other components (4).
- Known hypersensitivity to papayas or papain because of the risk of cross-sensitivity (4).

5 WARNINGS AND PRECAUTIONS

- Hypersensitivity reactions: Serious hypersensitivity reactions, including anaphylaxis, have been reported with postmarketing use of anacaulase-bcdb. If a hypersensitivity reaction occurs, remove NEXOBRID (if applicable) and initiate appropriate therapy (5.1).
- Coagulopathy: Avoid use of NEXOBRID in patients with uncontrolled disorders of coagulation. Use with caution in patients on anticoagulant therapy or other drugs affecting coagulation, and in patients with low platelet counts and increased risk of bleeding from other causes. Monitor patients for possible signs of coagulation abnormalities and signs of bleeding (5.2).

6 ADVERSE REACTIONS

The most common adverse reactions (>10%) were pruritus and pyrexia (6.1).

To report SUSPECTED ADVERSE REACTIONS, contact Vericel Corporation at 1-888-454-BURN or FDA at 1-800-FDA-1088 or www.fda.gov/medwatch.

FULL PRESCRIBING INFORMATION

1 INDICATIONS AND USAGE

NEXOBRID is indicated for eschar removal in adults and pediatric patients with deep partial thickness (DPT) and/or full thickness (FT) thermal burns.

Limitations of Use

The safety and effectiveness of NEXOBRID have not been established for treatment of:

- Chemical or electrical burns
- Burns on the face, perineum, or genitalia
- Burns on the feet of patients with diabetes mellitus or on the feet of patients with occlusive vascular disease
- Circumferential burns
- Burns in patients with significant cardiopulmonary disease, including inhalation injury

NEXOBRID is not recommended for:

- Wounds contaminated with radioactive and other hazardous substances to avoid unforeseeable reactions with the product and an increased risk of spreading the noxious substance.
- Treatment of burn wounds where medical devices (e.g., implants, pacemakers, shunts) or vital structures (e.g., large vessels) could become exposed during eschar removal.

2 DOSAGE AND ADMINISTRATION

2.1 Important Administration Information

NEXOBRID is only to be administered by a healthcare provider. Take precautions to avoid exposure to NEXOBRID during preparation and handling (e.g., use gloves, surgical masks, other protective coverings, as needed) [see Warnings and Precautions (5.1)].
Use pain management as practiced for an extensive dressing change of burn wounds 15 minutes prior to and throughout all NEXOBRID-related procedures.
NEXOBRID is available as:

- 2 g of lyophilized powder (containing 1.94 grams of anacaulase-bcdb) with a 20 g gel vehicle, for treatment of up to 180 cm^2 of burn area after mixing.
- 5 g lyophilized powder (containing 4.85 grams of anacaulase-bcdb) with a 50 g gel vehicle, for treatment of up to 450 cm^2 of burn area after mixing.

NEXOBRID lyophilized powder and gel vehicle must be mixed no more than 15 minutes prior to administration. Discard NEXOBRID if not used within 15 minutes of preparation, as the enzymatic activity of the product decreases progressively following mixing.

Each vial of lyophilized powder, jar of gel vehicle, and the mixed NEXOBRID are for use for only one patient and for one application [see Dosage and Administration (2.4)].

NEXOBRID is for topical use only.

Apply an ointment skin protectant around the treatment area to create an ointment barrier [see Dosage and Administration (2.3)].

2.2 Recommended Dosage

Recommended Dosage in Adults
Apply a 3 mm thick layer (approximate thickness of a tongue depressor) of NEXOBRID to a burn wound area of up to 15% body surface area (BSA) in one application in adult patients. Remove NEXOBRID after 4 hours [see Dosage and Administration (2.5)].
A second application of NEXOBRID may be applied 24 hours following the first application to either the same area previously treated with NEXOBRID or to a new area in adult patients. Apply a second application if:

- The wound area is more than 15% BSA, or
- Multiple wound areas on different body surfaces require two treatments for logistical reasons such as body position, or
- The first application's eschar removal was not complete.

For both applications, the total treated area must not exceed 20% BSA.

Recommended Dosage in Pediatric Patients
Pediatric Patients 6 Years of Age and Older
Apply a 3 mm thick layer (approximate thickness of a tongue depressor) of NEXOBRID to a burn wound area of up to 15% BSA in one application in pediatric patients 6 years of age and older. Remove NEXOBRID after 4 hours [see Dosage and Administration (2.5)]. A second application of NEXOBRID is not recommended.
Pediatric Patients Less Than 6 Years of Age
Apply a 3 mm thick layer (approximate thickness of a tongue depressor) of NEXOBRID to a burn wound area of up to 10% BSA in one application in pediatric patients less than 6 years of age. Remove NEXOBRID after 4 hours [see Dosage and Administration (2.5)]. A second application of NEXOBRID is not recommended.

2.3 Preparation of Patient and Burn Wound Treatment Area

Prepare the wound area as follows:

1. Thoroughly clean the wound to remove any charred tissue, blisters, and any topical products.
2. Apply a dressing soaked with an antibacterial solution to the treatment area for at least 2 hours.
3. Ensure the wound bed is clear of any remnants of topical agents (e.g., silver sulfadiazine, povidone iodine).
4. Apply an ointment skin protectant (e.g., petrolatum) 2 to 3 cm outside of the treatment area to create an ointment barrier. Avoid applying the protectant ointment to the treatment area itself, as this would impede direct contact of NEXOBRID with the eschar.
5. Protect any other open wounds (e.g., laceration, abraded skin, escharotomy incision) with skin protectant ointments or ointment gauze to prevent possible exposure to NEXOBRID.

2.4 Preparation and Application of NEXOBRID

Gather the following sterile supplies prior to NEXOBRID preparation and application:

- Instrument for mixing (e.g., spatula or tongue depressor)
- Tongue depressor for NEXOBRID application
- 0.9% Sodium Chloride Irrigation
- Occlusive film dressing
- Loose, thick fluffy dressing and bandage

Preparation
Prepare NEXOBRID at the patient’s bedside within 15 minutes of the intended application.
Using aseptic technique, mix NEXOBRID lyophilized powder and gel vehicle as follows:

1. Pour the NEXOBRID lyophilized powder into the gel vehicle jar.
2. Thoroughly mix the NEXOBRID lyophilized powder and gel vehicle using a sterile instrument (e.g., tongue depressor or spatula) until the mixture is uniform. The mixed lyophilized powder and gel vehicle produce NEXOBRID in a final concentration of 8.8% w/w.

DISCARD NEXOBRID IF NOT USED WITHIN 15 MINUTES OF PREPARATION, as the enzymatic activity of NEXOBRID decreases progressively following mixing.

Application
Apply NEXOBRID within 15 minutes of preparation as follows:

1. Moisten the treatment area by sprinkling sterile 0.9% Sodium Chloride Irrigation onto the burn wound.
2. Using a sterile tongue depressor, completely cover the moistened burn wound treatment area with the mixed NEXOBRID in a 3 mm thick layer (approximate thickness of a tongue depressor). Ensure NEXOBRID covers the entire target treatment area.
3. Cover the treated wound with a sterile occlusive film dressing.
4. Gently press the occlusive film dressing at the area of contact with the ointment barrier to ensure adherence between the occlusive film dressing and the ointment barrier and to achieve complete containment of NEXOBRID on the treatment area. There should be no visible air under the occlusive film dressing.
5. Cover the occlusive film dressing with a sterile loose, thick, fluffy dressing and secure with a sterile bandage.
6. Discard any unused portions of NEXOBRID.

2.5 Removal of NEXOBRID

Remove NEXOBRID after 4 hours. Gather the following sterile supplies prior to NEXOBRID removal:

- Blunt-edged instruments (e.g., tongue depressor)
- Large dry gauze
- Gauze soaked with 0.9% Sodium Chloride Irrigation
- Dressing soaked with an antibacterial solution

1. Remove the occlusive film dressing using aseptic technique.
2. Remove the ointment barrier using a sterile blunt-edged instrument.
3. Remove the dissolved eschar from the wound by scraping it away with a sterile blunt-edged instrument.
4. Wipe the wound thoroughly with a large sterile dry gauze, then wipe with a sterile gauze that has been soaked with sterile 0.9% Sodium Chloride Irrigation. Rub the treated area until the appearance of a clean dermis or subcutaneous tissues with pinpoint bleeding.
5. To remove remnants of dissolved eschar, apply a dressing soaked with an antibacterial solution for at least 2 hours.

2.6 Monitoring

Monitor patients for signs of local or systemic allergic reactions. If a hypersensitivity reaction occurs, remove NEXOBRID (if applicable) from the treatment area and initiate appropriate therapy [see Contraindications (4), Warnings and Precautions (5.1)].

3 DOSAGE FORMS AND STRENGTHS

For topical gel: 8.8%; off-white to light tan lyophilized powder in a glass vial to be mixed in a clear and colorless gel vehicle in a glass jar.

4 CONTRAINDICATIONS

NEXOBRID is contraindicated in patients with [see Warnings and Precautions (5.1), Description (11)]:

- Known hypersensitivity to anacaulase-bcdb, bromelain, pineapples, or to any of the other components.
- Known hypersensitivity to papayas or papain because of the risk of cross-sensitivity.

5 WARNINGS AND PRECAUTIONS

5.1 Hypersensitivity Reactions

NEXOBRID-Treated Patients

Serious hypersensitivity reactions, including anaphylaxis, have been reported with postmarketing use of NEXOBRID. If a hypersensitivity reaction occurs, remove NEXOBRID (if applicable) and initiate appropriate therapy.

NEXOBRID is contraindicated in patients with a known hypersensitivity to anacaulase- bcdb, bromelain, pineapples or to any other component of NEXOBRID. NEXOBRID is also contraindicated in patients with known hypersensitivity to papayas or papain because of the risk of cross-sensitivity.

Healthcare Providers Preparing and Applying NEXOBRID

Healthcare personnel should take appropriate precautions to avoid exposure when preparing and handling NEXOBRID (e.g., gloves, surgical masks, other protective coverings, as needed). In the event of inadvertent skin exposure, rinse NEXOBRID off with water to reduce the likelihood of skin sensitization.

5.2 Coagulopathy

A reduction of platelet aggregation and plasma fibrinogen levels and a moderate increase in partial thromboplastin and prothrombin times have been reported in the literature as possible effects following oral administration of bromelain, a component of NEXOBRID. In vitro and animal data suggest that bromelain can also promote fibrinolysis.
Avoid use of NEXOBRID in patients with uncontrolled disorders of coagulation. Use NEXOBRID with caution in patients on anticoagulant therapy or other drugs affecting coagulation, and in patients with low platelet counts and increased risk of bleeding from other causes (e.g., peptic ulcers and sepsis). Monitor patients for possible signs of coagulation abnormalities and signs of bleeding.

6 ADVERSE REACTIONS

The following clinically significant adverse reactions are described elsewhere in the labeling:

- Hypersensitivity Reactions [see Warnings and Precautions (5.1)]

6.1 Clinical Trials Experience

Because clinical trials are conducted under widely varying conditions, adverse reaction rates observed in the clinical trials of a product cannot be directly compared to rates in the clinical trials of another product and may not reflect the rates observed in practice.

Adults:
Studies 1 and 2 evaluated subjects undergoing eschar removal for deep partial thickness (DPT) and/or full thickness (FT) thermal burns [see Clinical Studies (14)]. An integrated analysis of safety data from Studies 1 and 2 compared NEXOBRID (n=177) to standard of care (SOC) (n=149). The SOC treatment included both surgical and non-surgical eschar removal methods.
The mean age of the safety population was 35.6 years; 73% were male; 81% were White, 9% were Black, 6% were other races, and 3% were Asian. Regarding burn etiology, 65% had fire/flame burns, 26% had scald burns, 8% had contact burns, and <1% had burns of other etiology. The mean body surface area (BSA) of wounds that received study treatment was 9.2±5.07%. Mean BSA of all burn wounds was 12.0±6.05%. Of the 177 subjects who were treated with NEXOBRID in Studies 1 and 2, 159 (90%) received one treatment of NEXOBRID, and 18 (10%) received 2 treatments.
Table 1 presents adverse reactions that occurred in ≥ 1% of subjects in the NEXOBRID arm and at a higher incidence than the SOC arm, up to 3 months following wound closure.

Table 1: Adverse Reactions Reported in ≥1% and Greater Incidence than Standard of Care in NEXOBRID-Treated Patients in Studies 1 and 2a
 | NEXOBRID (N = 177) Patients n (%) | Standard of Careb (N = 149) Patients n (%)
Pruritus | 27 (15) | 19 (13)
Pyrexia | 21 (12) | 13 (9)
Wound complicationc | 15 (9) | 9 (6.0)
Anemia | 11 (6) | 8 (5)
Vomiting | 9 (5) | 4 (3)
Insomnia | 8 (5) | 6 (4)
Urinary tract infection | 7 (4) | 1 (1)
Tachycardia | 5 (3) | 0
Rash | 6 (3) | 0
Infection | 4 (2) | 2 (1)
Sepsis | 4 (2) | 1 (1)
Leukocytosis | 3 (2) | 1 (1)
Hypotension | 3 (2) | 1 (1)
Hepatic function abnormal | 2 (1) | 0
Drug hypersensitivity | 2 (1) | 0
Bacteremia | 2 (1) | 0
Scar | 2 (1) | 0
Subcutaneous hematoma | 2 (1) | 0
Decubitus ulcer | 2 (1) | 0
a During the time period from baseline to 3 months post wound closure
b Standard of Care treatment included both surgical and non-surgical eschar removal methods
c Wound complication includes skin graft failure, graft loss, graft complication, and wound decomposition

Pediatric Subjects:
Study 3 (CIDS study) evaluated pediatric subjects undergoing eschar removal for deep partial thickness (DPT) and/or full thickness (FT) thermal burns [see Clinical Studies (14)]. A total of 139 subjects (69 NEXOBRID, 70 SOC) were treated in the study. The SOC treatment included both surgical and non-surgical eschar removal methods.
The mean age was comparable in the NEXOBRID (5.89 years) and SOC (5.75 years) arms. The majority of subjects were male (59% NEXOBRID, 69% SOC). For race, 70% NEXOBRID and 69% SOC subjects were White, 25% NEXOBRID and 23% SOC subjects were Asian, 4% NEXOBRID and 3% SOC subjects were Black or African American, and 1% NEXOBRID and 4% SOC subjects were other races. For ethnicity, 4% NEXOBRID and 10% SOC subjects identified as Hispanic or Latino. The majority of burns in both treatment arms (NEXOBRID and SOC) were due to scald (68% and 67%). The majority of patients in both treatment groups (NEXOBRID and SOC) had 1 treated wound (71% and 80%, respectively).
Table 2 presents adverse reactions that occurred in ≥ 1% of subjects in the NEXOBRID arm and at a higher incidence than the SOC arm, up to 3 months following wound closure.

Table 2: Adverse Reactions Reported in ≥1% and Greater Incidence than Standard of Care in NEXOBRID-Treated Pediatric Subjects in Study 3a
 | NEXOBRID (N = 69) Patients n (%) | Standard of Careb (N = 70) Patients n (%)
Pruritus | 9 (13) | 7 (10)
Pyrexia | 7 (10) | 4 (6)
Vomiting | 5 (7) | 3 (4)
Nausea | 3 (4) | 2 (3)
Constipation | 3 (4) | 1 (1)
Nasopharyngitis | 3 (4) | 1 (1)
Rash | 2 (3) | 0
Hemoglobin decreased | 2 (3) | 0
Rhinovirus | 2 (3) | 0
Ear Infection | 2 (3) | 0
a During the time period from baseline to 3 months post wound closure
b Standard of Care treatment included both surgical and non-surgical eschar removal methods

6.2 Postmarketing Experience

The following adverse reactions have been identified during postapproval use of anacaulase-bcdb outside of the United States. Because these reactions are reported voluntarily from a population of uncertain size, it is not always possible to reliably estimate their frequency or establish a causal relationship to drug exposure.

Immune system disorders: Hypersensitivity, including anaphylaxis and urticaria

8 USE IN SPECIFIC POPULATIONS

8.1 Pregnancy

Risk Summary

There are no available data on NEXOBRID use in pregnant women to evaluate for a drug associated risk of major birth defects, miscarriage, or other adverse maternal or fetal outcomes.

The background risk of major birth defects and miscarriage for the indicated population is unknown. All pregnancies have a background risk of birth defect, loss, or other adverse outcomes. In the U.S. general population, the estimated background risk of major birth defects and miscarriage in clinically recognized pregnancies is 2 to 4% and 15 to 20%, respectively.

Data

Animal Data

In embryofetal developmental studies in rats and rabbits, intravenous doses up to 4 and 0.1 mg/kg/day NEXOBRID were administered to pregnant rats and rabbits, respectively, during organogenesis. No significant developmental toxicities were observed in these studies. However, severe maternal toxicities were noted and the tolerable maternal exposure levels were much lower compared with the maximum human exposure in clinical setting.

8.2 Lactation

Risk Summary

There are no data on the presence of anacaulase-bcdb in either human or animal milk, the effects on the breastfed infant, or the effects on milk production. The developmental and health benefits of breastfeeding should be considered along with the mother’s clinical need for NEXOBRID and any potential adverse effects on the breastfed infant from NEXOBRID or from the underlying maternal condition.

8.4 Pediatric Use

The safety and effectiveness of NEXOBRID for eschar removal have been established in pediatric patients with deep partial thickness and/or full thickness thermal burns. Use of NEXOBRID for this indication is supported by evidence from one adequate and well-controlled trial in 69 pediatric subjects treated with NEXOBRID [see Clinical Studies (14)].

8.5 Geriatric Use

Of the 177 subjects exposed to NEXOBRID for eschar removal in deep partial thickness (DPT) and/or full thickness (FT) thermal burns, 6 (3%) subjects were 65 years or older, and 1 (< 1%) subject was 75 years or older [see Clinical Studies (14)]. Clinical trials of NEXOBRID did not include sufficient numbers of subjects 65 years of age and older to determine whether they respond differently from younger adult subjects.

11 DESCRIPTION

The drug substance in NEXOBRID, anacaulase-bcdb, is a mixture of proteolytic enzymes extracted from the stems of pineapple plants (Ananas comosus [L.] Merr.) that has been sterile filtered and lyophilized. The drug substance, anacaulase-bcdb, is composed mainly (80% to 95% w/w) of the proteins: stem bromelain, ananain, jacalin-like lectin, bromelain inhibitors, and phytocystatin inhibitor; and saccharides, as both free monosaccharides and the N-linked glycan of stem bromelain, and small molecule metabolites. The drug substance includes inactive buffer components containing acetic acid, ammonium sulfate, and Water for Injection. Each gram of lyophilized powder contains 0.97 grams of anacaulase-bcdb.

NEXOBRID (anacaulase-bcdb) for topical gel is a botanical drug product supplied as a sterile, preservative-free, lyophilized powder in a single-dose glass vial that must be mixed in a gel vehicle supplied in a single-dose glass jar prior to application. Mixture of either 2 grams of lyophilized powder (containing 1.94 grams of anacaulase-bcdb) or 5 grams of lyophilized powder (containing 4.85 grams of anacaulase-bcdb) in 20 grams or 50 grams of gel vehicle, respectively, provides an 8.8% w/w, yellowish white to light brown opaque gel for topical use. The pH of the topical gel mixture is approximately 6.2 to 6.7.

The co-packaged 20 gram or 50 gram jar of the sterile, preservative-free gel vehicle contains carbomer 980, dibasic sodium phosphate, sodium hydroxide, and Water for Injection.

12 CLINICAL PHARMACOLOGY

12.1 Mechanism of Action

The mixture of enzymes in NEXOBRID dissolves burn wound eschar. The specific components responsible for this effect have not been identified.

12.2 Pharmacodynamics

The pharmacodynamics of NEXOBRID are unknown.

Cardiac Electrophysiology

At the approved recommended dose, NEXOBRID did not prolong the QT interval in humans to any clinically relevant extent.

12.3 Pharmacokinetics

Absorption

For adults and pediatric subjects 4 years of age and older, NEXOBRID applied to deep partial and full thickness burn wounds is absorbed, with median serum Tmax of 4 hours (during the treatment application). Systemic exposure (i.e., AUC) of bromelain, a component of anacaulase-bcdb is correlated with the size of the treated area and NEXOBRID dose, but not the depth of the burn wound. The systemic exposure in pediatric subjects was comparable to adults.
In adult subjects, Cmax and the dose‑normalized Cmax values after the first and second application (mean dosing interval of 17 hours) are comparable and only slight accumulation (less than 2-fold difference) is seen in AUC0-4 and AUC0-4 dose‑normalized levels after the second application, compared to the first application.

Elimination

A majority of adults and pediatric subjects had no quantifiable serum concentrations after 72 hours. The mean ± SD terminal half-life of bromelain, a component of anacaulase-bcdb, is 12 ± 4.4 hours.

Drug Interaction Studies

Effect of NEXOBRID on Other Drugs

Bromelain, a component of anacaulase-bcdb, exhibited CYP2C8 time-dependent inhibition in human hepatocytes and inhibited human microsomal CYP2C9. No clinical studies have been conducted to assess the potential for systemic drug interactions.

12.6 Immunogenicity

There is insufficient information to characterize the anti-drug antibody response to anacaulase- bcdb and the effects of anti-drug antibodies on pharmacokinetics, pharmacodynamics, safety, or effectiveness of NEXOBRID.

13 NONCLINICAL TOXICOLOGY

13.1 Carcinogenesis, Mutagenesis, Impairment of Fertility

Carcinogenicity or fertility studies have not been conducted with anacaulase-bcdb.

Anacaulase-bcdb was not genotoxic in a bacterial reverse mutation assay and an in vitro mammalian chromosome aberration assay.

14 CLINICAL STUDIES

14.1 Adults

The efficacy of NEXOBRID for the eschar removal of deep partial thickness (DPT) and full thickness (FT) thermal burns has been investigated in two trials.

Study 1
NEXOBRID was investigated in the DETECT randomized, controlled, assessor-blinded, three-arm trial, comparing NEXOBRID, standard of care (SOC), and gel vehicle treatment in subjects with DPT and/or FT thermal burns of 3 - 30% BSA (Study 1, NCT02148705). SOC included both surgical and non-surgical methods for eschar removal per the investigators’ discretion. Subjects on the NEXOBRID and gel vehicle arms who had eschar remaining following the topical treatment period were treated with SOC. NEXOBRID was compared to gel vehicle for the incidence of ≥95% eschar removal at the end of the topical treatment period. NEXOBRID was also compared with SOC for the incidence of surgical eschar removal (tangential, minor, avulsion, Versajet and/or dermabrasion excision) and time to eschar removal.
A total of 175 subjects were randomized in a 3:3:1 ratio (NEXOBRID : SOC : gel vehicle) and 169 subjects were treated. The mean age was 41 years, 70% of subjects were male and 30% were female, and 81% were White, 14% were Black or African American, 5% were other races, and 1% were Asian. Seventeen percent of subjects were Hispanic or Latino. Subjects had one or more target wounds (TWs) to be treated for eschar removal. The mean percentage BSA of all TWs per subject was 6.1%. The majority of subjects (82%) had one to two TWs.
The incidence of ≥95% eschar removal at the end of the topical treatment period for subjects in the NEXOBRID and gel vehicle groups is shown in Table 3.

Table 3: Incidence of ≥95% Eschar Removal at the End of the Topical Treatment Period in NEXOBRID- or Gel Vehicle-Treated Subjects (Study 1; DETECT)
NEXOBRID (N=75) | Gel Vehicle (N=25) | Treatment Difference (95% Confidence Interval)
93% (70/75) | 4% (1/25) | 89% (74%, 96%)

The incidence of surgical eschar removal (tangential, minor, avulsion, Versajet and/or dermabrasion excision) and time to ≥95% eschar removal for the NEXOBRID and SOC groups are shown in Table 4.

Table 4: Incidence of Excision for Eschar Removal in NEXOBRID- or SOC-Treated Subjects (Study 1; DETECT)
NEXOBRID (N=75) | SOC (N=75) | Treatment Difference (95% Confidence Interval)
4% (3/75) | 72% (54/75) | -68% (-78%, -56%)
SOC = standard of care

The median time to eschar removal was 1 day on the NEXOBRID arm and 3.8 days on the SOC arm.
The estimated median time to ≥95% wound closure for all TWs on a subject was 31 days for the NEXOBRID arm and 36 days for the SOC treatment arm. Subjects were not evaluated frequently enough after achieving ≥95% wound closure to adequately assess time to 100% wound closure.
Study 2
NEXOBRID was investigated in a multicenter, open-label, randomized, two-arm trial, comparing NEXOBRID to SOC treatment in subjects with DPT and/or FT thermal burns of 5 - 24% BSA (Study 2; NCT00324311). SOC included both surgical and non-surgical methods for eschar removal per the investigators’ discretion. The trial enrolled 182 subjects. The first subject at each site (26 subjects) was not randomized and was treated with NEXOBRID. The remaining 156 subjects were randomized to NEXOBRID or SOC. The efficacy assessments were analyzed on DPT burns only.
Demographics were similar across both arms. The mean age was 29.9 years. Approximately 80% of the study subjects were adults (≥18 years), 74% were male and 26% were female, 82% were White, 7% were other races, 6% were Black, and 5% were Asian.
The incidence of surgical eschar removal (tangential, minor, avulsion, Versajet and/or dermabrasion excision) for the NEXOBRID and SOC groups is shown in Table 5.

Table 5: Incidence of Excision of Eschar Removal of Deep Partial Thickness Wounds in Patients with Thermal Burns (Study 2)
 | NEXOBRID N=106 Wounds in 49 Subjectsa | SOC N=88 Wounds in 48 Subjectsa | Treatment Difference (95% Confidence Interval)
Incidence of excision for eschar removal (per wound)b | 15% 16/106 wounds | 63% 55/88 wounds | -47% (-59%, -34%)
Incidence of excision for eschar removal (per subject)b, c | 22% 11/49 subjects | 77% 37/48 subjects | -55% (-71%, -38%)
SOC = standard of care
aAnalysis population includes only patients with at least one wound that was entirely DPT
bSurgical eschar removal procedures include (tangential, minor, avulsion, Versajet and/or dermabrasion excision)
cAssessement per subject was an exploratory analysis

In randomized subjects, the estimated median time to ≥95% wound closure was 33 days for the NEXOBRID arm and 24 days for the SOC treatment arm. Subjects were not evaluated frequently enough after achieving ≥95% wound closure to adequately assess time to 100% wound closure.

14.2 Pediatric Subjects

Study 3
NEXOBRID was investigated in the CIDS study which was an open label, randomized, controlled, two arm trial comparing NEXOBRID and standard of care (SOC) treatment in subjects 7 months to 18 years of age with DPT and/or FT thermal burns of ≥1% - 30% BSA (Study 3, NCT02278718). SOC included both surgical and nonsurgical methods for eschar removal per the investigator’s discretion. Subjects on the NEXOBRID arm who had eschar remaining following the topical treatment period were treated with SOC. NEXOBRID was compared with SOC for the time to eschar removal and for the incidence of surgical eschar removal (tangential, minor, avulsion, Versajet and/or dermabrasion excision).
A total of 145 subjects were randomized in a 1:1 ratio (NEXOBRID:SOC) and 139 subjects were treated. The mean age was approximately 6 years, with a median of 3.4 years in the NEXOBRID group and 3.9 years in the SOC group. In the trial, 62% were male, 70% were White, 23% were Asian, 4% were Black or African American, and 3% were other races; for ethnicity, 7% identified as Hispanic or Latino. Subjects had one or more target wounds (TWs) to be treated for eschar removal. The mean percentage BSA of all TWs per subject was 5.6%. The majority of subjects in both treatment groups had 1 TW (71.0% for NEXOBRID and 80.0% for SOC).
The median time to ≥95% eschar removal is shown in Table 6.

Table 6: Time to ≥95% Eschar Removal, Estimated Median Time for NEXOBRID vs SOC in Pediatric Subjects (Study 3; CIDS)
 | NEXOBRID (N=72) | SOC (N=73)
Median (Days) 95% Confidence Interval | 0.99 (0.88, 1.04) | 5.99 (2.71, 9.84)

The incidence of surgical eschar removal (tangential, minor, avulsion, Versajet and/or dermabrasion excision) is shown in Table 7.

Table 7: Incidence of Surgical Excision for Eschar Removal for NEXOBRID vs SOC in Pediatric Subjects (Study 3; CIDS)
NEXOBRID (N=72) | SOC (N=73) | Treatment Difference (95% Confidence Interval)
8% (6/72) | 64% (47/73) | -56% (-68%, -42%)

The estimated median time to ≥95% wound closure for all target wounds on a subject was 32 days for the NEXOBRID arm and 34 days for the SOC treatment arm. The estimated median time reach 100% wound closure on a target wound level was 44 days for NexoBrid arm and 43 days for the SOC arm.

16 HOW SUPPLIED/STORAGE AND HANDLING

How Supplied

NEXOBRID (anacaulase-bcdb) for topical gel, 8.8%, is supplied as a package containing two components, a sterile, preservative-free, off-white to light tan lyophilized powder in a glass vial and a sterile, preservative-free, clear and colorless gel vehicle in a glass jar, that are mixed prior to application [see Dosage and Administration (2.4)].

NEXOBRID is available:

- One glass vial of 2 g lyophilized powder (containing 1.94 grams of anacaulase-bcdb) and one glass jar of 20 g gel vehicle per carton (NDC 69866-2002-3)
- One glass vial of 5 g lyophilized powder (containing 4.85 grams of anacaulase-bcdb) and one glass jar of 50 g gel vehicle per carton (NDC 69866-2005-3)

Storage and Handling

Store and transport NEXOBRID package upright and refrigerated at 2℃ to 8℃ (36 ℉ to 46 ℉) in the original carton to protect from light. DO NOT FREEZE.

Do not use if the vial or jar are damaged.

17 PATIENT COUNSELING INFORMATION

Hypersensitivity Reactions

Advise patients of the risk of hypersensitivity reactions, including anaphylaxis [see Warnings and Precautions (5.1)].

Manufactured by:
Vericel Corporation
64 Sidney Street,
Cambridge, MA 02139
U.S. License number 2010

NEXOBRID® is a registered trademark of MediWound LTD.
L65629.6

PRINCIPAL DISPLAY PANEL - NDC: 69866-2002-3 - 2g/20g Carton Label

NexoBrid
(anacaulase-bcdb)
For topical gel, 8.8%
For Topical Use Only
Net weight is 22 grams (after mixing)
VERICEL®

PRINCIPAL DISPLAY PANEL - NDC: 69866-2005-3 - 5g/50g Carton Label

NexoBrid
(anacaulase-bcdb)
For topical gel, 8.8%
For Topical Use Only
Net weight is 55 grams (after mixing)
VERICEL®

PRINCIPAL DISPLAY PANEL - NDC: 69866-2015-3 - 5g/50g NFS Carton Label

NOT FOR SALE
NexoBrid
(anacaulase-bcdb)
For topical gel, 8.8%
For Topical Use Only
Net weight is 55 grams (after mixing)
VERICEL®